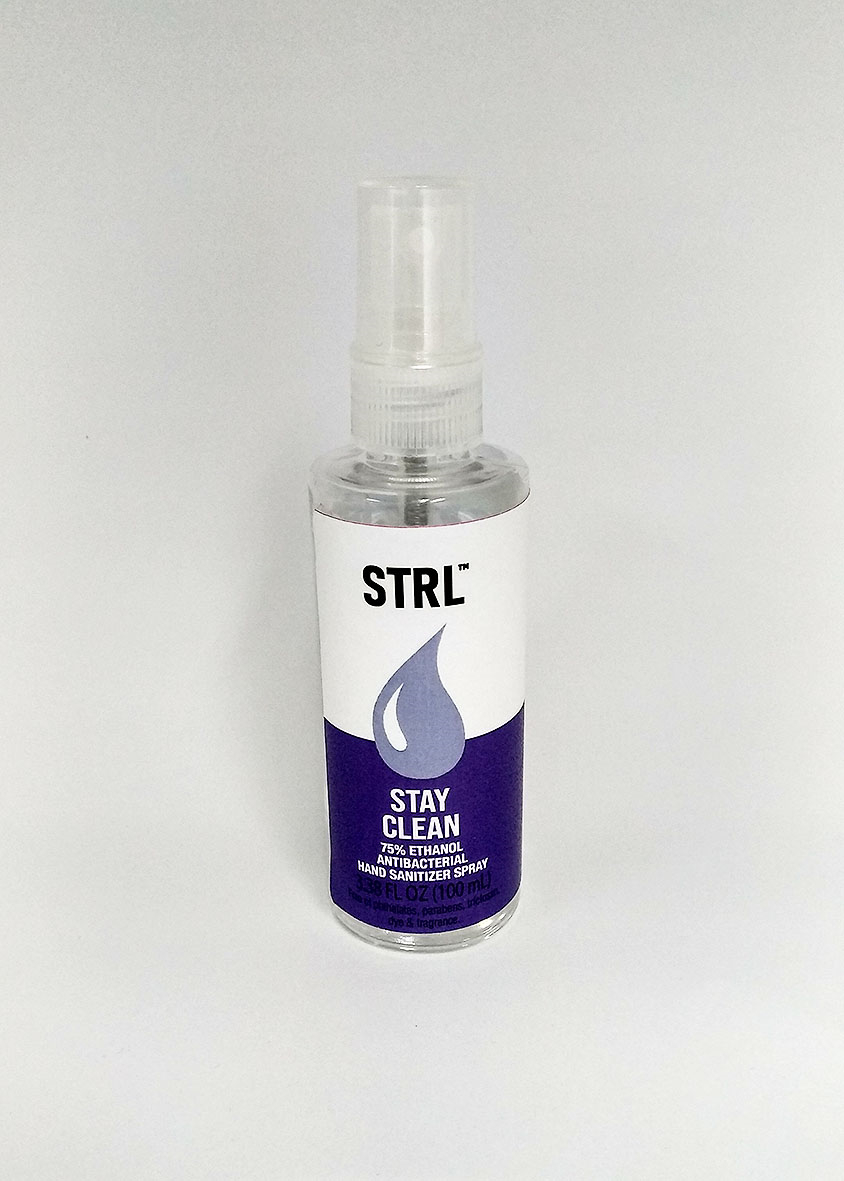 DRUG LABEL: STRL Stay Clean Hand Sanitizer
NDC: 66965-001 | Form: LIQUID
Manufacturer: WOWWEE GROUP LIMITED
Category: otc | Type: HUMAN OTC DRUG LABEL
Date: 20200520

ACTIVE INGREDIENTS: ALCOHOL 75 mL/100 mL
INACTIVE INGREDIENTS: WATER

DOSAGE AND ADMINISTRATION

Store in cool,dry place below 104°F(40°C)

INACTIVE INGREDIENT

water

INDICATIONS AND USAGE

1.Spray on clean, dry hands,nail and surfaces.

2.Wet hands or surfaces thoroughly.

3.Allow surfaces to dry without wiping.

4.Rub hands together briskly until dry.

5.For children under 6,use only under adult supervision.

6.Not recimmended for infants

ACTIVE INGREDIENT

Ethanol

keep out of reach of children

PURPOSE

Disinfection
Sterilization
No Rinseing

WARNINGS

Keep out of eyes.In case of contact with eyes, flush thoroughly with water.

Avoid contact with broken skin.

Do not inhale or ingest.
For extemal use only,Flammeble, keep away from fire or flame.